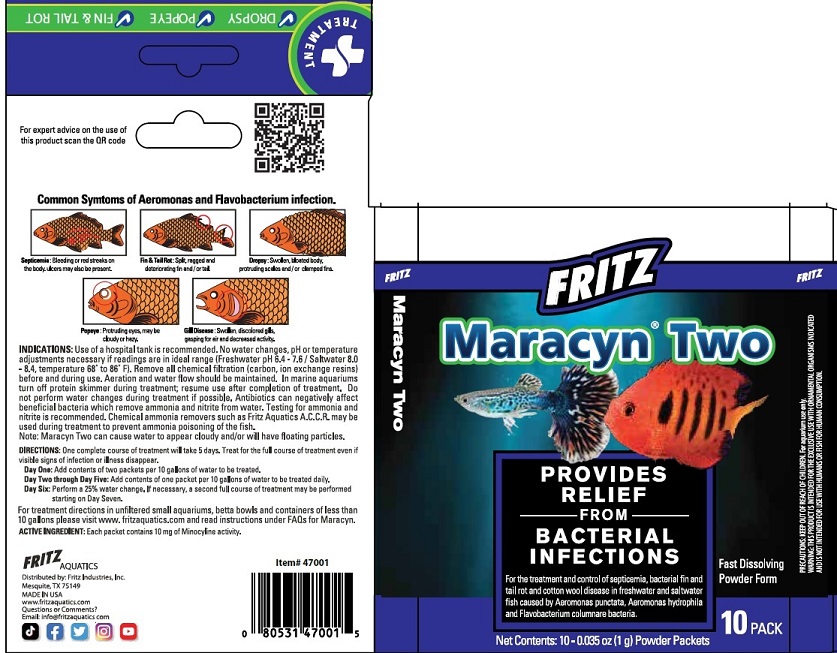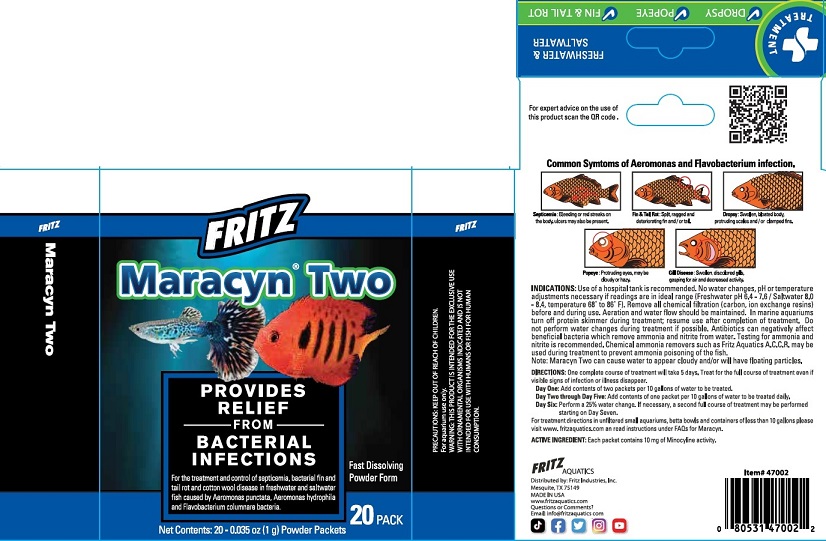 DRUG LABEL: Fritz Aquatics Mardel Maracyn Two
NDC: 53745-012 | Form: POWDER
Manufacturer: Fritz Industries
Category: animal | Type: OTC ANIMAL DRUG LABEL
Date: 20240108

ACTIVE INGREDIENTS: MINOCYCLINE 10 mg/0.6 g

fRITZ - Maracyn Two

ACTIVE INGREDIENT: Each packet contains 10 mg Minocycline activity.